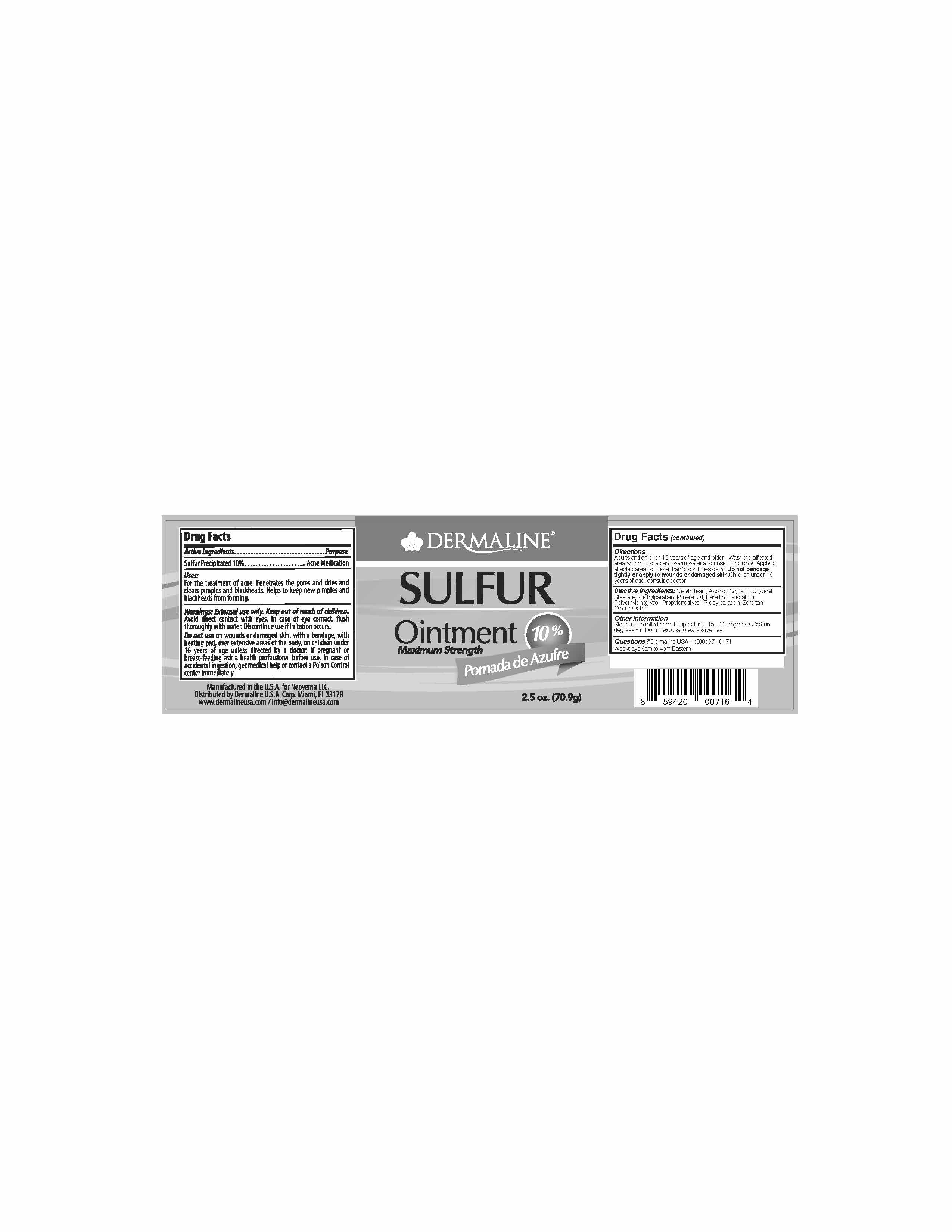 DRUG LABEL: Acne Treatment
NDC: 82165-108 | Form: OINTMENT
Manufacturer: Dermaline USA corp
Category: otc | Type: HUMAN OTC DRUG LABEL
Date: 20220708

ACTIVE INGREDIENTS: SULFUR 10 g/100 g
INACTIVE INGREDIENTS: GLYCERIN; GLYCERYL STEARATE SE; MINERAL OIL; PARAFFIN; PROPYLENE GLYCOL 2-PALMITATE; WATER; CETYL ALCOHOL; PEG-6 SORBITAN OLEATE; POLYETHYLENE GLYCOL 300; PROPYLPARABEN; METHYLPARABEN; PETROLATUM

Dermaline Sulfur

ACTIVE INGREDIENT

Sulfur Precipitated 10%....... Acne Medication

Uses:

For the treatment of acne. Penetrates the pores and dries and clears pimples and blackheads. Helps to keep new pimples and blackheads from forming.

KEEP OUT OF REACH OF CHILDREN

Warnings: External Use Only. Keep out of reach of children.

Avoid direct contact with eyes. In case of eye contact, flush thoroughly with water. Discontinue use if irritation occurs.

Do not use on wounds or damaged skin, with a bandage, with heating pad, over extensive areas of the body, on children under 16 years of age unless directed by a doctor. If pregnant or breast-feeding ask a health professional before use. In case of accidental ingestion, get medical help or contact a Poison Control center immediately.

WHEN USING

Adults and children 16 years of age and older. Wash th affected area with mild soap and warm water and rinse thorougly. Apply to affected area not more than 3 to 4 times daily. Do not bandage tightly or apply to wounds or damaged skin. Children under 16 years of age: consult a doctor.

INACTIVE INGREDIENT

Cetyl/Stearyl Alcohol, Glycerin, Glyceryl Stearate, Methylparaben, Mineral Oil, Paraffin, Petrolatum, Polyethyleneglycol, Propyleneglycol, Propylparaben, Sorbitan Oleate, Water

OTHER SAFETY INFORMATION

Store at controlled room temperature: 15- 30 degrees C (59-86 degree F). Do not expose to excessive heat.

QUESTIONS

Questions? Dermaline USA, 1(800) 371-0171 Weekdays 9am to 4pm. Eastern

DOSAGE AND ADMINISTRATION

Adults and children 16 years of age and older. Wash th affected area with mild soap and warm water and rinse thorougly. Apply to affected area not more than 3 to 4 times daily. Do not bandage tightly or apply to wounds or damaged skin. Children under 16 years of age: consult a doctor.

WARNINGS

Warnings: External Use Only. Keep out of reach of children.

Avoid direct contact with eyes. In case of eye contact, flush thoroughly with water. Discontinue use if irritation occurs.

Uses:

For the treatment of acne. Penetrates the pores and dries and clears pimples and blackheads. Helps to keep new pimples and blackheads from forming.

PURPOSE

Acne Medication

Label